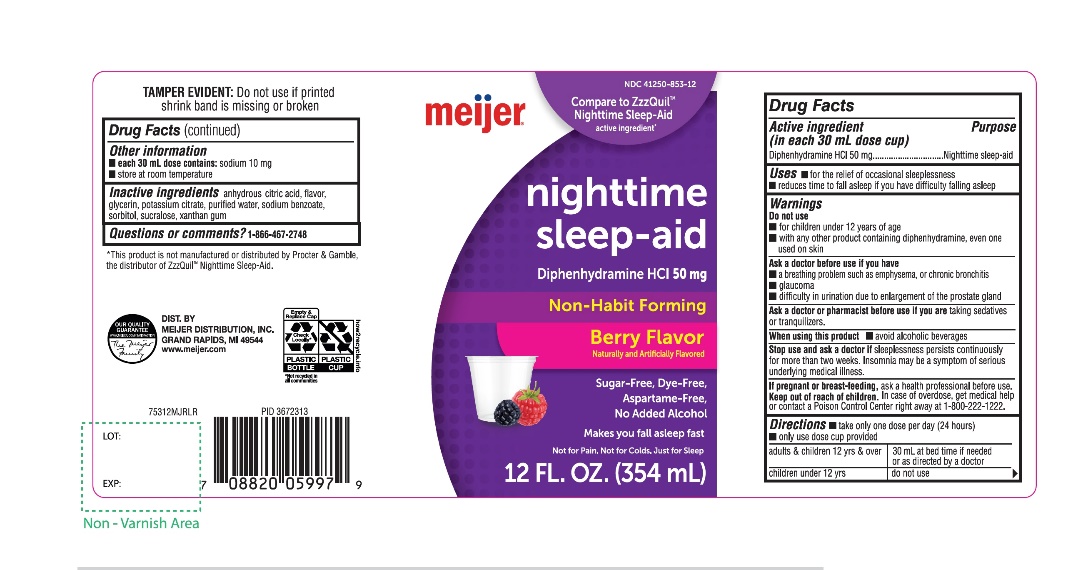 DRUG LABEL: Meijer Nighttime Sleep Aid

NDC: 41250-853 | Form: LIQUID
Manufacturer: MEIJER DISTRIBUTION INC
Category: otc | Type: HUMAN OTC DRUG LABEL
Date: 20251024

ACTIVE INGREDIENTS: DIPHENHYDRAMINE HYDROCHLORIDE 50 mg/30 mL
INACTIVE INGREDIENTS: ANHYDROUS CITRIC ACID; GLYCERIN; POTASSIUM CITRATE; WATER; SODIUM BENZOATE; SORBITOL; SUCRALOSE; XANTHAN GUM

Meijer Nighttime Sleep Aid Berry Flavor 12 FL OZ (354 mL)

Drug Facts

Active ingredient (in each 30 mL)

Diphenhydramine HCl 50 mg

Purpose

Nighttime sleep-aid

Uses

- for the relief of occasional sleeplessness
- reduces time to fall asleep if you have difficulty falling asleep

Warnings

Do not use

- for children under 12 years of age
- with any other product containing diphenhydramine, even one used on skin

Ask a doctor before use if you have

- a breathing problem such as emphysema, or chronic bronchitis
- glaucoma
- difficulty in urination due to enlargement of the prostate gland

Ask a doctor or pharmacist before use if you aretaking sedatives or tranquilizers

When using this product

- avoid alcoholic beverages

Stop use and ask a doctor ifsleeplessness persists continuously for more than two weeks. Insomnia may be a symptom of serious underlying medical illness.

PREGNANCY OR BREAST FEEDING

If pregnant or breast-feeding, ask a health professional before use.

Keep out of reach of children.

In case of overdose, get medical help or contact a Poison Control Center right away at 1-800-222-1222.

Directions

- take only one dose per day (24 hours)
- measure with dosing cup provided

1. adults & children 12 yrs & over

1. 30 mL at bed time if needed or as directed by a doctor

1. children under 12 yrs

1. do not use

Other information

- each 30 mL dose contains:sodium 10 mg
- store at room temperature

Inactive ingredients

anhydrous citric acid, flavor, glycerin, potassium citrate, purified water, sodium benzoate, sorbitol, sucralose, xanthan gum.

Questions or comments?

1-866-467-2748

PRINCIPAL DISPLAY PANEL

meijer®

Compare to ZzzQuil®Nighttime Sleep-Aid active ingredient*

NDC# 41250-853-12

Nighttime sleep-aid

Diphenhydramine HCl 50 mg

Non-Habit Forming

Berry Flavor

Naturally and Artificially Flavored

Sugar-Free, Dye-Free, Aspartame-Free, Alcohol-Free

Makes you fall asleep fast

Not for Pain. Not for Colds. Just for Sleep

12 FL OZ (354 mL)

TAMPER EVIDENT: Do not use if printed shrink band is missing or broken

OUR QUALITY GUARANTEE

WWW.MEIJER.COM/SATISFACTION

DIST. BY MEIJER DISTRIBUTION, INC.

GRANDS RAPIDS, MI 49544

www.meijer.com